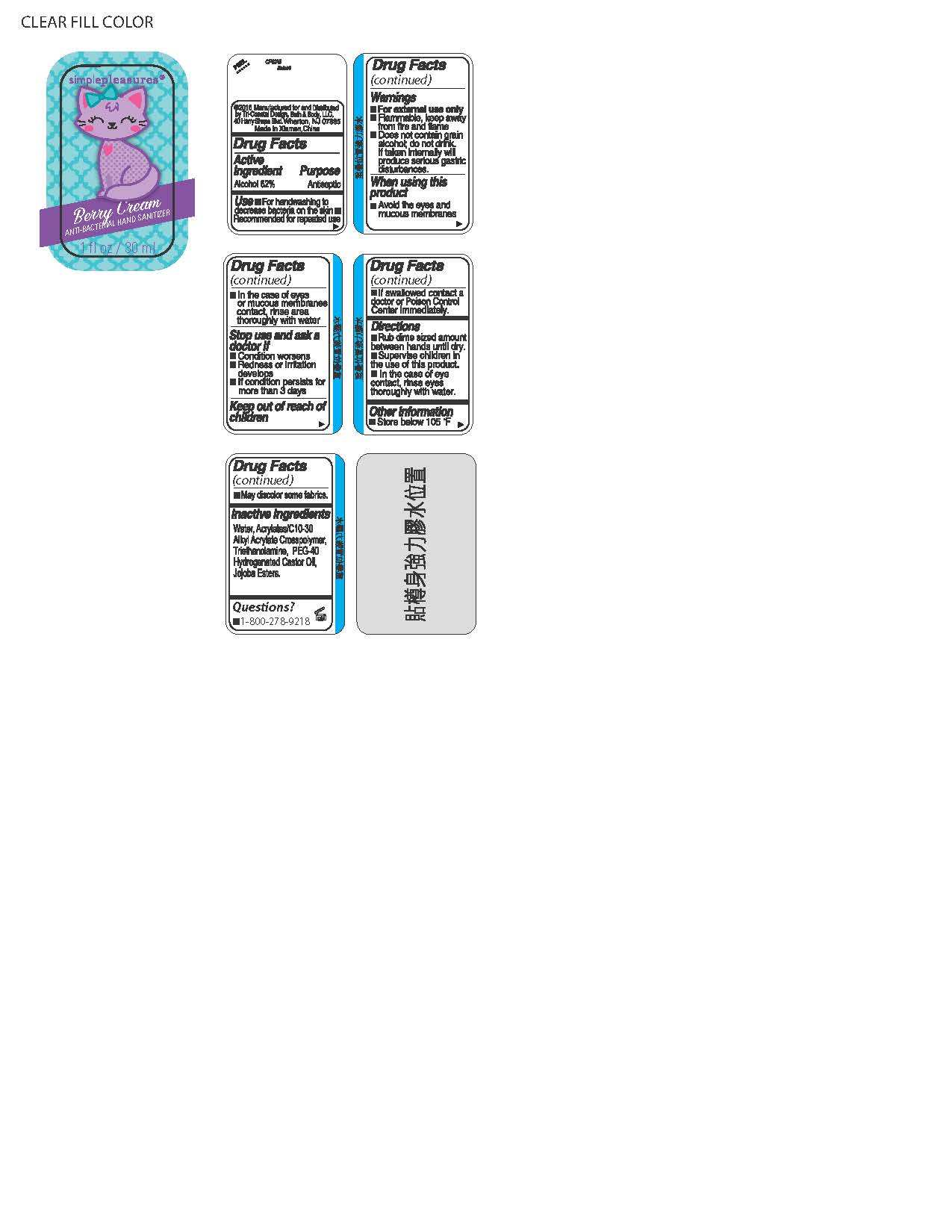 DRUG LABEL: ANTI BACTERIAL HAND SANITIZER
NDC: 49852-304 | Form: LIQUID
Manufacturer: Tri-Coastal Design Company Inc.
Category: otc | Type: HUMAN OTC DRUG LABEL
Date: 20171206

ACTIVE INGREDIENTS: ALCOHOL 62 g/100 mL
INACTIVE INGREDIENTS: WATER; CARBOMER INTERPOLYMER TYPE A (ALLYL SUCROSE CROSSLINKED); TROLAMINE; POLYOXYL 40 HYDROGENATED CASTOR OIL; HYDROLYZED JOJOBA ESTERS (ACID FORM)

Drug Facts

Active Ingredient

Alcohol 62%

Purpose

Antiseptic

Use

- For handwashing to decrease bacteria on the skin
- Recommended for repeated use

Warnings

- For external use only
- Flammable, keep away from fire and flame
- Does not contain grain alcohol; do not drink, if taken internally will produce serious gastric disturbances

When using this product

- Avoid the eyes and mucous membranes
- In the case of eyes or mucous membrane contact; rinse area thoroughly with water

Stop use and ask a doctor if

- Condition worsens
- Redness or irritation develops
- If condition persists for more than 3 days

Keep out of reach of children

- If swallowed contact a doctor or Poison Control Center immediately.

Directions

- Rub dime sized amount between hands until dry.
- Supervise children in the use of this product.
- In the case of eye contact, rinse eyes thoroughly with water.

Other information

- Store below 105F
- May discolor some fabrics

Inactive Ingredients

Water, Acrylates/C10-30 Alkyl Acrylate Crosspolymer, Triethanolamine, PEG-40 Hydrogenated Castor Oil, Jojoba Esters

Questions?

- 1-800-278-9218